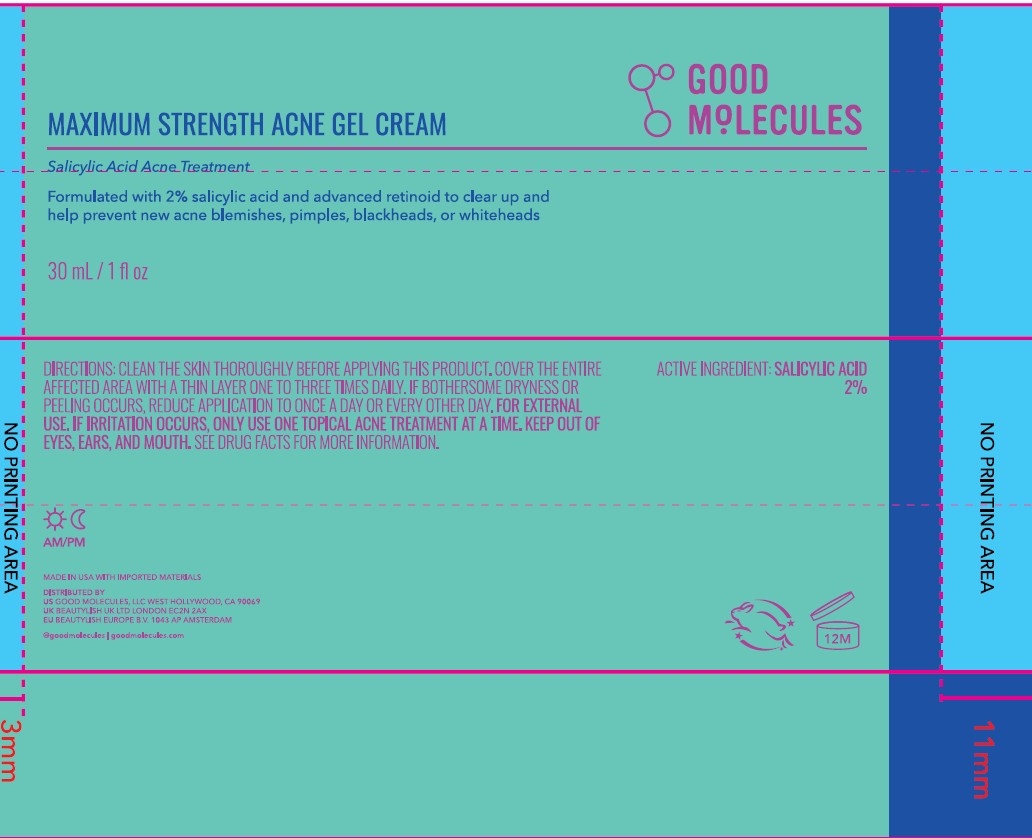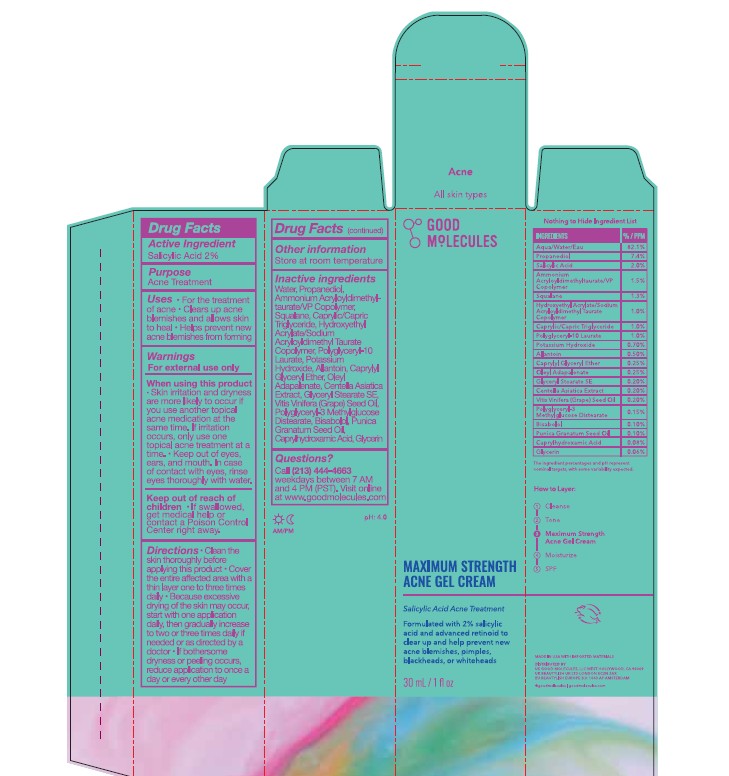 DRUG LABEL: GOOD MOLECULE MAXIMUM STRENGHT ACNE
NDC: 68577-231 | Form: GEL
Manufacturer: COSMAX USA, CORP
Category: otc | Type: HUMAN OTC DRUG LABEL
Date: 20251223

ACTIVE INGREDIENTS: SALICYLIC ACID 2 mg/100 mL
INACTIVE INGREDIENTS: PROPANEDIOL; CAPRYLYL GLYCOL; GLYCERYL STEARATE SE; POLYGLYCERYL-3 METHYLGLUCOSE DISTEARATE; CAPRYLOYL GLYCERIN/SEBACIC ACID COPOLYMER (2000 MPA.S); WATER; GLYCERIN; PUNICA GRANATUM SEED OIL; BISABOLOL; DIGLUCOSYL GALLIC ACID; CAPRYLHYDROXAMIC ACID; AMMONIUM ACRYLOYLDIMETHYLTAURATE/VP COPOLYMER; HYDROXYETHYL ACRYLATE/SODIUM ACRYLOYLDIMETHYL TAURATE COPOLYMER (45000 MPA.S AT 1%); POLYGLYCERYL-10 LAURATE; SODIUM HYDROXIDE; CAPRYLYL GLYCERYL ETHER; CENTELLA ASIATICA TRITERPENOIDS; VITIS VINIFERA (GRAPE) SEED OIL; ALLANTOIN; DIHEPTYL SUCCINATE

GOOD MOLECULES MAXIMUM STRENGTH ACNE GEL CREAM

Active Ingredients

Salicylic Acid 2%

Purpose

Acne Treatment

USES

- For the treatment of acne
- Clears up acne blemishes and allows skin to heal
- Helps prevent new acne blemishes from forming

Warnings

For external use only

When using this product

- Skin irritation and dryness ae more likely to occur if you use another topical acne medication at the same time. If irritation occurs, onlyuse one topical acne treatment at a time.
- Keep out of eyes, ears, and mouth. In case of contact with eyes, rinse eyes thoroughly with water.

Keep out of reach of children

- If swallowed, get medical help or contact a Poison Control Center right away

DIRECTIONS

- Clean skin thoroughly before applying this product
- Cover the entire affected area with a thin layer one to three times daily
- Because excessive drying of the skin may occur, start with one application daily, then gradually increase to two of three times daily if needed or as directed by a doctor.
- If bothersome dryness or peeling occurs, reduce application to once a day or every other day.

OTHER INFORMATION

Store at room temperature

Inactive ingredients

Water, Propanediol, Diheptyl Succinate, Glycerin, Ammonium Acryloyldimethyltaurate/VP Copolymer, Hydroxyethyl Acrylate/Sodium Acryloyldimethyl Taurate Copolymer, Polyglyceryl-10 Laurate, Sodium Hydroxide, Caprylyl Glycol, Caprylyl Glyceryl Ether, Glyceryl Stearate SE, Vitis Vinifera (Grape) Seed Oil, Polyglyceryl-3 Methylglucose Distearate, Centella Asiatica Extract, Allantoin, Bisabolol, Punica Granatum Seed Oil, Diglucosyl Gallic Acid, Caprylhydroxamic Acid, and Capryloyl Glycerin/Sebacic Acid Copolymer.